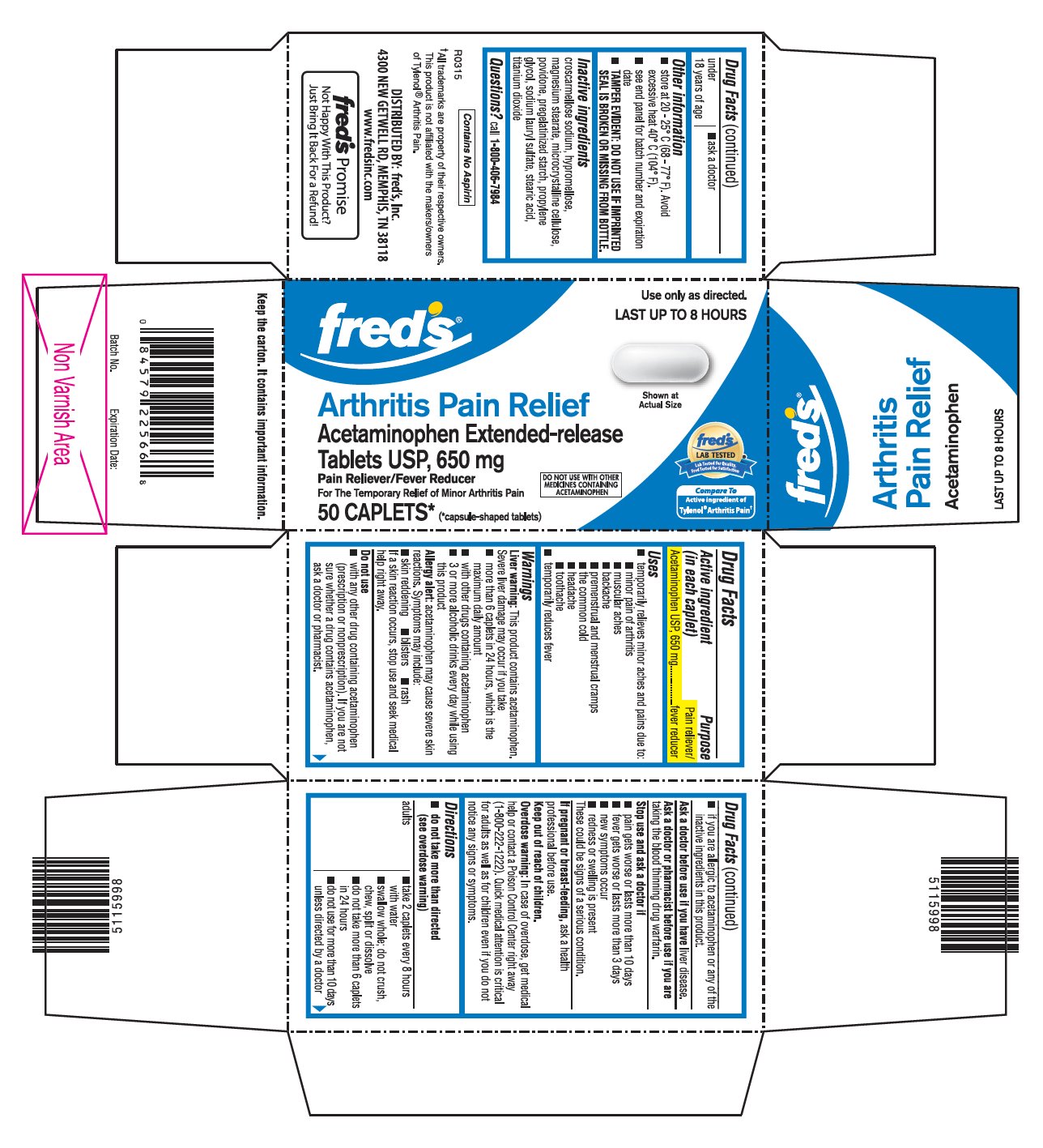 DRUG LABEL: Acetaminophen
NDC: 55315-333 | Form: TABLET, FILM COATED, EXTENDED RELEASE
Manufacturer: Fred's Inc.
Category: otc | Type: HUMAN OTC DRUG LABEL
Date: 20191224

ACTIVE INGREDIENTS: ACETAMINOPHEN 650 mg/1 1
INACTIVE INGREDIENTS: CROSCARMELLOSE SODIUM; MAGNESIUM STEARATE; PROPYLENE GLYCOL; SODIUM LAURYL SULFATE; STEARIC ACID; TITANIUM DIOXIDE; HYPROMELLOSE, UNSPECIFIED; MICROCRYSTALLINE CELLULOSE; POVIDONE, UNSPECIFIED; STARCH, CORN

Drug Facts

ACTIVE INGREDIENT (IN EACH CAPLET)

Acetaminophen USP, 650 mg

PURPOSE

Pain reliever/fever reducer

USES

- temporarily relieves minor aches and pains due to:
  - minor pain of arthritis
  - muscular aches
  - backache
  - premenstrual and menstrual cramps
  - the common cold
  - headache
  - toothache
- temporarily reduces fever

WARNINGS

Liver warning: This product contains acetaminophen. Severe liver damage may occur if you take

- more than 6 caplets in 24 hours, which is the maximum daily amount
- with other drugs containing acetaminophen
- 3 or more alcoholic drinks every day while using this product

Allergy alert: acetaminophen may cause severe skin reactions. Symptoms may include:

- Skin reddening
- Blisters
- Rash

If a skin reaction occurs, stop use and seek medical help right away.

Do not use

- with any other drug containing acetaminophen (prescription or nonprescription). If you are not sure whether a drug contains acetaminophen, ask a doctor or pharmacist.
- if you are allergic to acetaminophen or any of the inactive ingredients in this product.

Ask a doctor before use if you have

Liver disease.

Ask a doctor or pharmacist before use if you are

taking the blood thinning drug warfarin.

Stop use and ask a doctor if

- pain gets worse or lasts more than 10 days
- fever gets worse or lasts more than 3 days
- new symptoms occur
- redness or swelling is present

These could be signs of a serious condition.

If pregnant or breast-feeding

Ask a health professional before use.

Keep out of reach of children.

Overdose warning: In case of overdose, get medical help or contact a Poison Control Center right away (1-800-222-1222). Quick medical attention is critical for adults as well as for children even if you do not notice any signs or symptoms.

DIRECTIONS

- do not take more than directed (see overdose warning)

adults | ▪ take 2 caplets every 8 hours with water ▪ swallow whole - do not crush, chew, split or dissolve ▪ do not take more than 6 caplets in 24 hours ▪ do not use for more than 10 days unless directed by a doctor
under 18 years of age | ▪ ask a doctor

OTHER INFORMATION

- store at 20 - 25° C (68 - 77° F). Avoid excessive heat 40° C (104° F).
- see end panel for batch number and expiration date
- TAMPER EVIDENT: DO NOT USE IF IMPRINTED SEAL IS BROKEN OR MISSING FROM BOTTLE.

INACTIVE INGREDIENTS

Croscarmellose sodium, hypromellose, magnesium stearate, microcrystalline cellulose, povidone, pregelatinized starch, propylene glycol, sodium lauryl sulfate, stearic acid, titanium dioxide

QUESTIONS?

Call 1-800-406-7984

PRINCIPAL DISPLAY PANEL

fred's®

Use only as directed.

LAST UP TO 8 HOURS

Arthritis Pain Relief

Acetaminophen Extended-Release Tablets USP, 650 mg

Pain Reliever/Fever Reducer

For The Temporary Relief of Minor Arthritis Pain

DO NOT USE WITH OTHER MEDICINES CONTAINING ACETAMINOPHEN

50 CAPLETS* (*capsule-shaped tablets)

Compare To Active Ingredient of Tylenol® Arthritis Pain†

DISTRIBUTED BY: fred's, Inc.